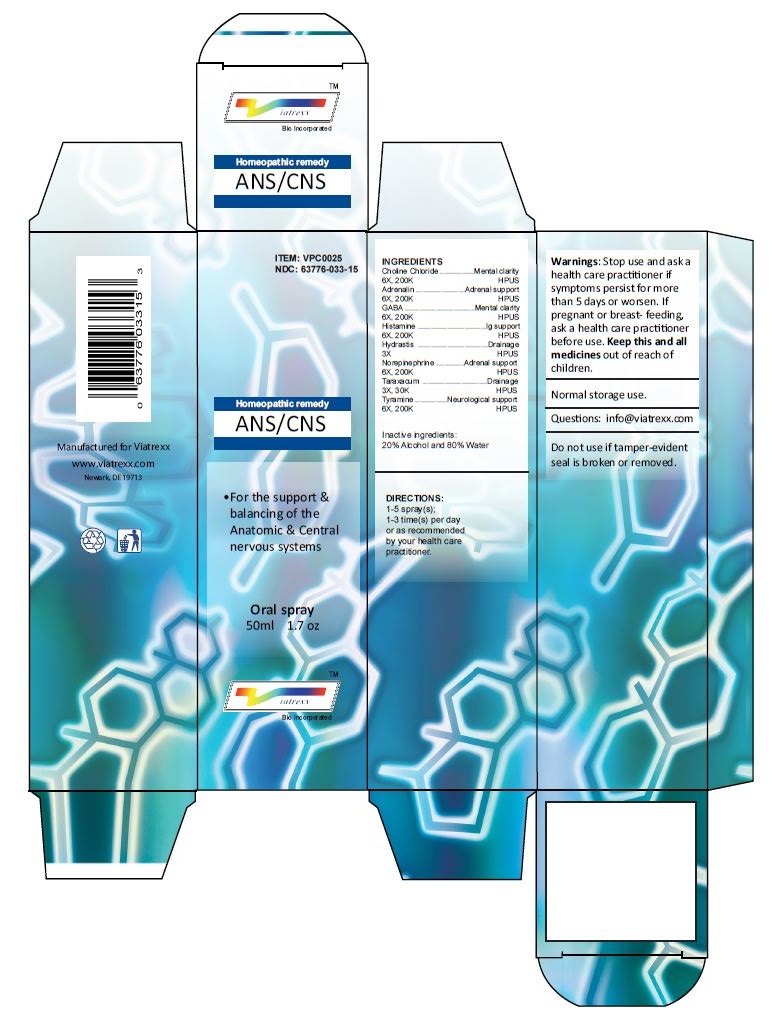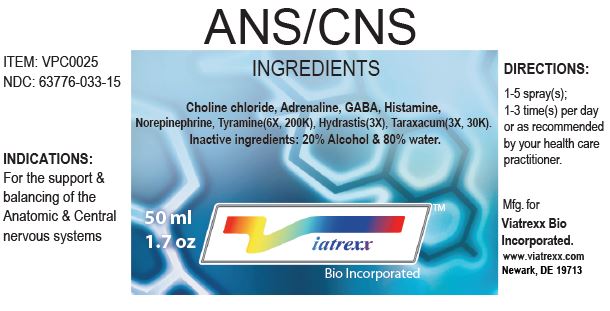 DRUG LABEL: ANS/CNS
NDC: 63776-033 | Form: SPRAY
Manufacturer: VIATREXX BIO INCORPORATED
Category: homeopathic | Type: HUMAN OTC DRUG LABEL
Date: 20221130

ACTIVE INGREDIENTS: CHOLINE CHLORIDE 200 [kp_C]/1 mL; EPINEPHRINE 200 [kp_C]/1 mL; .GAMMA.-AMINOBUTYRIC ACID 200 [kp_C]/1 mL; HISTAMINE 200 [kp_C]/1 mL; GOLDENSEAL 3 [hp_X]/1 mL; NOREPINEPHRINE 200 [kp_C]/1 mL; TARAXACUM PALUSTRE ROOT 30 [kp_C]/1 mL; TYRAMINE 200 [kp_C]/1 mL
INACTIVE INGREDIENTS: ALCOHOL; WATER

ANS/CNS

Active Ingredients

Choline Chloride 6X 200K, Adrenalin 6X 200K, GABA 6X 200K, Histamine 6X 200K, Hydrastis 3X, Norepinephrine 6X 200K, Taraxacum 3X 30K, Tyramine 6X 200K

Purpose:

Choline Chloride | Mental clarity
Adrenalin | Adrenal support
GABA | Mental clarity
Histamine | Ig support
Hydrastis | Drainage
Norepinephrine | Adrenal support
Taraxacum | Drainage
Tyramine | Neurological support

Uses

For the support & balancing of the Anatomic & Central nervous systems

Warnings

Stop use and ask a health care practitioner if symptoms persist for more than five days or worsen. If pregnant or breastfeeding, ask a health care practitioner before use.

Dosage

1-5 spray(s); 1-3 time(s) per day or as recommended by your health care practitioner.

KEEP OUT OF REACH OF CHILDREN

Keep this and all medicines out of reach of children.

Other Ingredients

Alcohol and Water

Other Information

Normal storage use.
Do not use if tamper-evident seal is broken or removed.

Questions

info@viatrexx.com

Principal Display Panel

ITEM: VPC0025
NDC 63776-033-15
Homeopathic remedy
ANS/CNS
• For the support & balancing of the Anatomic & Central nervous systems
Oral spray
50ml 1.7 oz
Viatrexx™ Bio Incorporated
Manufactured by Viatrexx
www.viatrexx.com
Newark, DE 19713

ANS/CNS
50 mL
1.7 oz
Viatrexx™ Bio Incorporated
ITEM: VPC0025
NDC: 63776-033-15
INDICATIONS:
For the support & balancing of the Anatomic & Central nervous systems
DIRECTIONS:
1-5 spray(s); 1-3 time(s) per day or as recommended by your health care practitioner.
Mfg. for
Viatrexx Bio Incorporated.
www.viatrexx.com
Newark, DE 19713